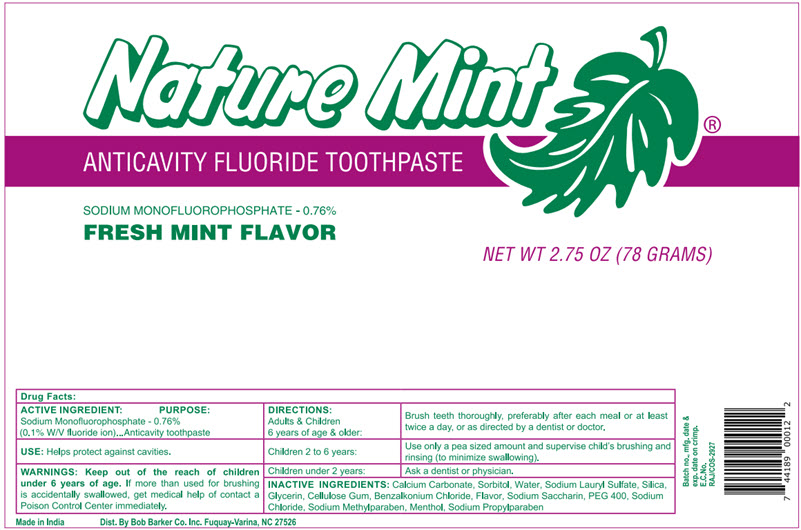 DRUG LABEL: Nature Mint Anticavity
NDC: 53247-144 | Form: PASTE, DENTIFRICE
Manufacturer: Bob Barker Company Inc.
Category: otc | Type: HUMAN OTC DRUG LABEL
Date: 20251020

ACTIVE INGREDIENTS: Sodium Monofluorophosphate 7.6 mg/1 g
INACTIVE INGREDIENTS: Calcium Carbonate; Sorbitol; Water; Sodium Lauryl Sulfate; Silicon Dioxide; Glycerin; Carboxymethylcellulose Sodium, Unspecified; Benzalkonium Chloride; Saccharin Sodium; POLYETHYLENE GLYCOL 400; Sodium Chloride; Methylparaben Sodium; Menthol, Unspecified Form; Propylparaben Sodium

Nature Mint® Anticavity

Drug Facts:

ACTIVE INGREDIENT

Sodium Monofluorophosphate - 0.76% (0.1% W/V fluoride ion)

PURPOSE

Anticavity toothpaste

USE

Helps protect against cavities.

WARNINGS

KEEP OUT OF REACH OF CHILDREN

Keep out of the reach of children under 6 years of age. If more than used for brushing is accidentally swallowed, get medical help of contact a Poison Control Center immediately.

DIRECTIONS

Adults & Children 6 years of age & older: | Brush teeth thoroughly, preferably after each meal or at least twice a day, or as directed by a dentist or doctor.
Children 2 to 6 years: | Use only a pea sized amount and supervise child's brushing and rinsing (to minimize swallowing).
Children under 2 years: | Ask a dentist or physician.

INACTIVE INGREDIENTS

Calcium Carbonate, Sorbitol, Water, Sodium Lauryl Sulfate, Silica, Glycerin, Cellulose Gum, Benzalkonium Chloride, Flavor, Sodium Saccharin, PEG 400, Sodium Chloride, Sodium Methylparaben, Menthol, Sodium Propylparaben

Dist. By Bob Barker Co. Inc. Fuquay-Varina, NC 27526

PRINCIPAL DISPLAY PANEL - 78 Gram Tube Label

Nature Mint®

ANTICAVITY FLUORIDE TOOTHPASTE

SODIUM MONOFLUOROPHOSPHATE - 0.76%
FRESH MINT FLAVOR

NET WT 2.75 OZ (78 GRAMS)